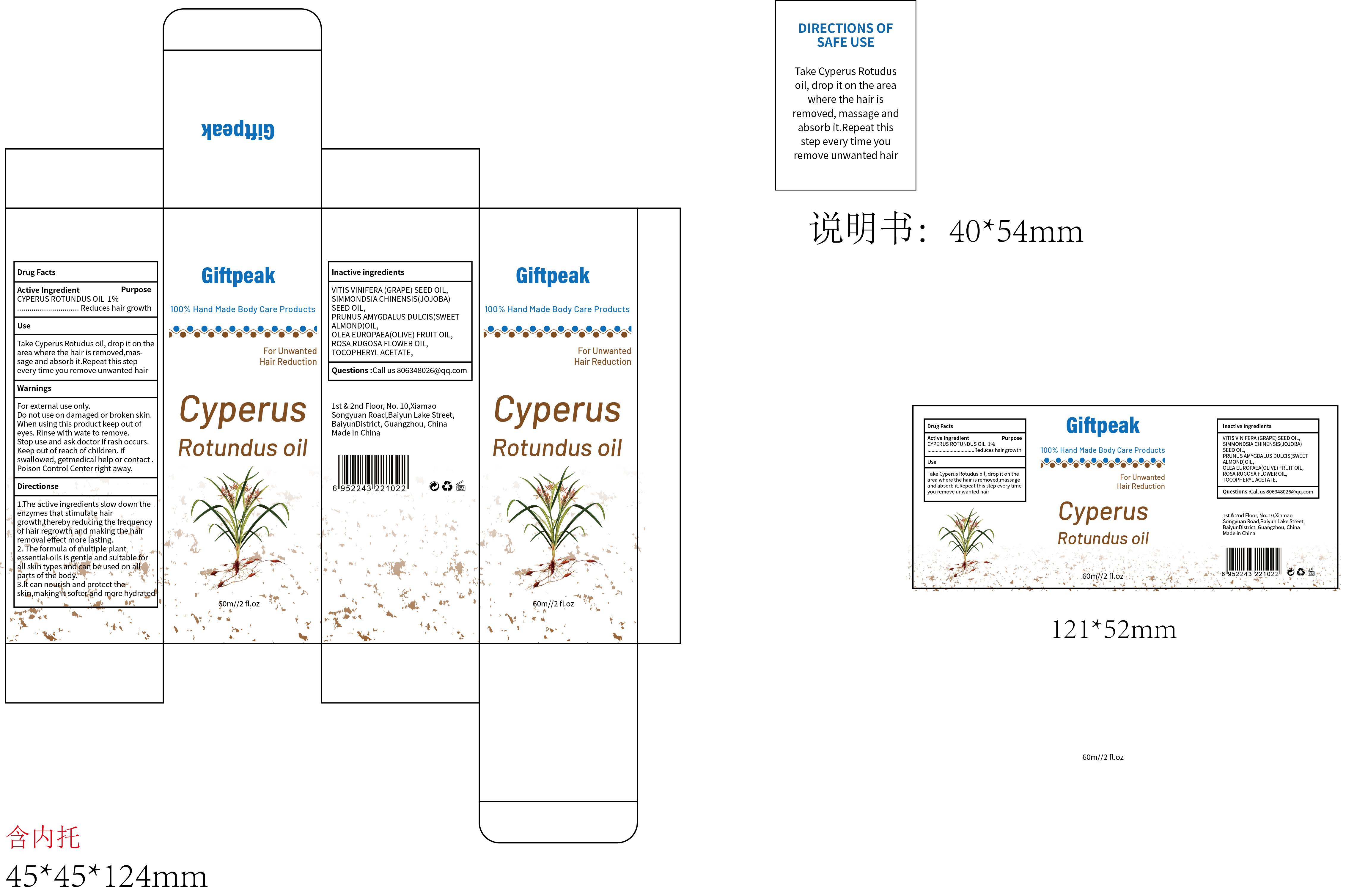 DRUG LABEL: Giftpeak Cyperus Rotundus oil
NDC: 60771-0006 | Form: OIL
Manufacturer: Guangzhou Haishi Biological Technology Co., Ltd.
Category: otc | Type: HUMAN OTC DRUG LABEL
Date: 20241109

ACTIVE INGREDIENTS: CYPERUS ROTUNDUS ROOT 1 g/100 mL
INACTIVE INGREDIENTS: ROSA RUGOSA FLOWER; SIMMONDSIA CHINENSIS (JOJOBA) SEED OIL; PRUNUS AMYGDALUS DULCIS (SWEET ALMOND) OIL; OLEA EUROPAEA (OLIVE) FRUIT OIL; VITIS VINIFERA (GRAPE) SEED OIL

Giftpeak Cyperus Rotundus oil

Active ingredients

CYPERUS ROTUNDUS OIL 1%

Purpose

For after hair removal care

Uses

DIRECTIONS OF SAFE USE:

Take Cyperus Rotudus oil, drop iton the area where the hair isremoved,massage and absorb it.Repeat this step every time youremove unwanted hair

Warnings

For external use only.

Stop use and ask a doctor if

rash occurs.

Do not use

on damaged or broken skin.

When using this product

keep out of eyes. Rinse with water to remove.

Keep out of reach of children.

If swallowed, get medical help or contact a Poison Control Center right away.

Dosage

Take a proper amount of Cyperus rotundus oil drop in the hair removal area, massage and absorb it

Inactive ingredients

VITIS VINIFERA (GRAPE) SEED OIL 80%
SIMMONDSIA CHINENSIS (JOJOBA) SEED OIL 10%
PRUNUS AMYGDALUS DULCIS (SWEET ALMOND) OIL 5%
OLEA EUROPAEA (OLIVE) FRUIT OIL 2%

ROSA RUGOSA FLOWER OIL 1%
TOCOPHERYL ACETATE 1%